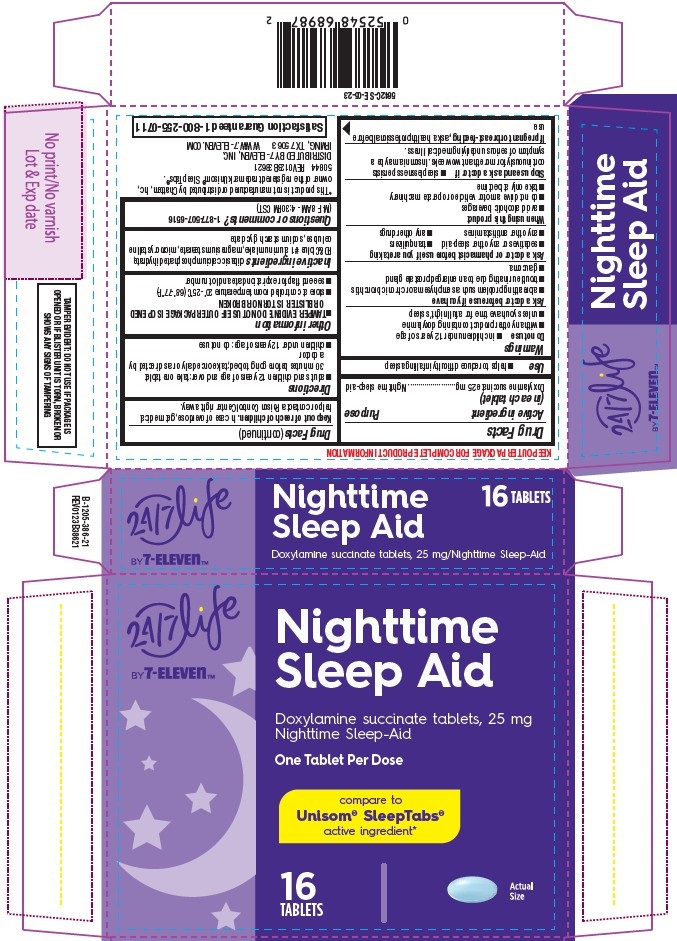 DRUG LABEL: Nighttime Sleep Aid, 24-7 Life by 7-Eleven
NDC: 66715-5642 | Form: TABLET
Manufacturer: Lil' Drug Store Products, Inc.
Category: otc | Type: HUMAN OTC DRUG LABEL
Date: 20251208

ACTIVE INGREDIENTS: DOXYLAMINE SUCCINATE 25 mg/1 1
INACTIVE INGREDIENTS: FD&C BLUE NO. 1 ALUMINUM LAKE; DIBASIC CALCIUM PHOSPHATE DIHYDRATE; MICROCRYSTALLINE CELLULOSE; SODIUM STARCH GLYCOLATE TYPE A POTATO; MAGNESIUM STEARATE

Nighttime Sleep Aid, 24/7 Life by 7-ElevenTM

Drug Facts

Active ingredient

Active ingredient (in each tablet)

Doxylamine succinate 25 mg

Purpose

Nighttime sleep-aid

Use

- helps to reduce difficulty in falling asleep

Warnings

Do not use

- in children under 12 years of age
- with any other product containing doxylamine
- unless you have time for a full night’s sleep

Ask a doctor before use if you have

- a breathing problem such as emphysema or chronic bronchitis
- trouble urinating due to an enlarged prostate gland
- glaucoma

Ask a doctor or pharmacist before use if you are taking

- sedatives or any other sleep-aid
- tranquilizers
- any other antihistamines
- any other drugs

When using this product

- avoid alcoholic beverages
- do not drive a motor vehicle or operate machinery
- take only at bedtime

Stop use and ask a doctor if

- sleeplessness persists continuously for more than two weeks. Insomnia may be a symptom of serious underlying medical illness.

If pregnant or breast-feeding, ask a health professional before use.

Keep out of reach of children. In case of overdose, get medical help or contact a Poison Control Center right away.

Directions

- adults and children 12 years of age and over: take one tablet 30 minutes before going to bed; take once daily or as directed by a doctor
- children under 12 years of age: do not use

Other information

- TAMPER EVIDENT: DO NOT USE IF OUTER PACKAGE IS OPENED OR BLISTER IS TORN OR BROKEN
- store at controlled room temperature 20°-25°C (68°-77°F)
- see end flap for expiration date and lot number

Inactive ingredients

dibasic calcium phosphate dihydrate, FD&C blue #1 aluminum lake, magnesium stearate, microcrystalline cellulose, sodium starch glycolate

Questions or comments?1-877-507-6516
(M-F 8AM - 4:30PM CST)

Nighttime Sleep Aid, 24/7 Life by 7-ElevenTM

[ 24/7 Life by 7-ElevenTMlogo]

Nighttime
Sleep Aid

Doxylamine succinate tablets, 25 mg
Nighttime Sleep-Aid

One Tablet Per Dose

compare to
Unisom® SleepTabs®
active ingredient*

16

TABLETS

[tablet image]

Actual

Size